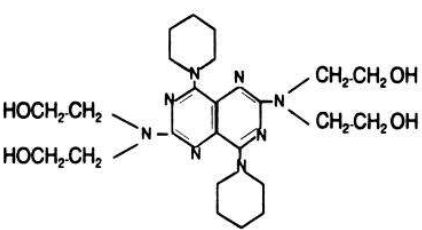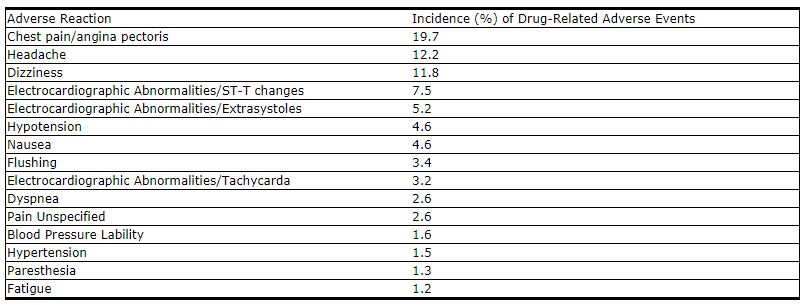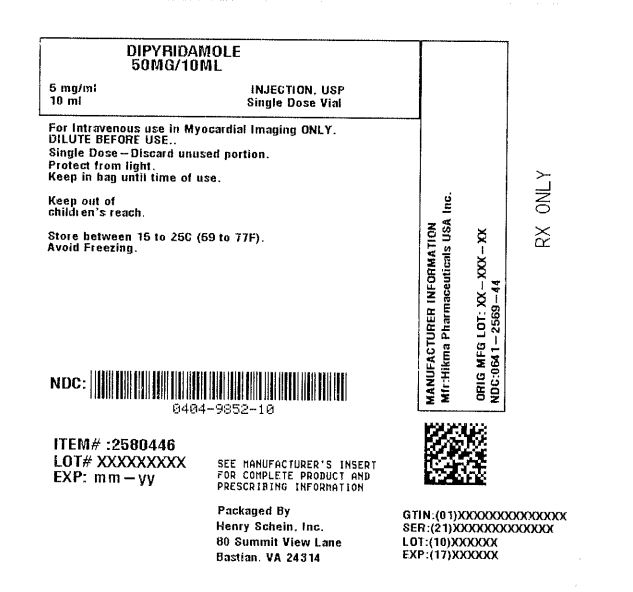 DRUG LABEL: Dipyridamole
NDC: 0404-9852 | Form: INJECTION
Manufacturer: Henry Schein, Inc.
Category: prescription | Type: HUMAN PRESCRIPTION DRUG LABEL
Date: 20251030

ACTIVE INGREDIENTS: Dipyridamole 5 mg/1 mL

Dipyridamole 5 mg/mL Injection, USP 10 mL Single Dose Vial

DESCRIPTION

Dipyridamole is a coronary vasodilator described as 2,6 bis-(diethanolamino)-4,8 dipiperidino-pyrimido-(5,4-d) pyrimidine. The structural formula is:

C24H40N8O4 MW 504.63
Dipyridamole Injection, USP is a sterile, odorless, pale yellow liquid which can be diluted in sodium chloride injection or dextrose injection for intravenous administration. Each mL contains 5 mg dipyridamole, USP, 50 mg polyethylene glycol 600 and 2 mg tartaric acid in Water for Injection, USP. pH 2.2-3.2; hydrochloric acid added for pH adjustment.

Clinical Pharmacology

In a study of 10 patients with angiographically normal or minimally stenosed (less than 25% luminal diameter narrowing) coronary vessels, Dipyridamole Injection in a dose of 0.56 mg/kg infused over 4 minutes resulted in an average fivefold increase in coronary blood flow velocity compared to resting coronary flow velocity (range 3.8 to 7 times resting velocity). The mean time to peak
flow velocity was 6.5 minutes from the start of the 4-minute infusion (range 2.5 to 8.7 minutes). Cardiovascular responses to the intravenous administration of Dipyridamole Injection when given to patients in the supine position include a mild but significant increase in heart rate of approximately 20% and mild but significant decreases in both systolic and diastolic blood pressure of approximately 2-8%, with vital signs returning to baseline values in approximately 30 minutes.

Mechanism of Action
Dipyridamole is a coronary vasodilator in man. The mechanism of vasodilation has not been fully elucidated, but may result from inhibition of uptake of adenosine, an important mediator of coronary vasodilation. The vasodilatory effects of dipyridamole are abolished by administration of the adenosine receptor antagonist theophylline. How dipyridamole-induced vasodilation leads to abnormalities in thallium distribution and ventricular function is also uncertain but presumably represents a “steal” phenomenon in which relatively intact vessels dilate and sustain enhanced flow, leaving reduced pressure and flow across areas of hemodynamically important coronary vascular constriction.

Pharmacokinetics and Metabolism
Plasma dipyridamole concentrations decline in a triexponential fashion following intravenous infusion of dipyridamole, with halflives averaging 3-12 minutes, 33-62 minutes and 11.6-15 hours. Two minutes following a 0.568 mg/kg dose of Dipyridamole Injection administered as a 4-minute infusion, the mean dipyridamole serum concentration is 4.6 ± 1.3 mcg/mL. The average plasma
protein binding of dipyridamole is approximately 99%, primarily toa1-glycoprotein. Dipyridamole is metabolized in the liver to the glucuronic acid conjugate and excreted with the bile. The average total body clearance is 2.3-3.5 mL/min/kg, with an apparent volume of distribution at steady state of 1-2.5 L/kg and a central apparent volume of 3-5 liters.

Indications and Usage

Dipyridamole Injection is indicated as an alternative to exercise in thallium myocardial perfusion imaging for the evaluation of coronary artery disease in patients who cannot exercise adequately.
In a study of about 1100 patients who underwent coronary arteriography and Dipyridamole Injection assisted thallium imaging, the results of both tests were interpreted blindly and the sensitivity and specificity of the dipyridamole thallium study in predicting the angiographic outcome were calculated. The sensitivity of the dipyridamole test (true positive dipyridamole divided by the total
number of patients with positive angiography) was about 85%. The specificity (true negative divided by the number of patients with negative angiograms) was about 50%. In a subset of patients who had exercise thallium imaging as well as dipyridamole thallium imaging, sensitivity and specificity of the two tests were almost identical.

Contraindications

Hypersensitivity to dipyridamole.

Warnings

Serious adverse reactions associated with the administration of intravenous Dipyridamole Injection have included cardiac death, fatal and non-fatal myocardial infarction, ventricular fibrillation, symptomatic ventricular tachycardia, stroke, transient cerebral ischemia, seizures, anaphylactoid reaction and bronchospasm. There have been reported cases of asystole, sinus node arrest, sinus node depression and conduction block. Patients with abnormalities of cardiac impulse formation/conduction or severe coronary artery disease may be at increased risk for these events.
In a study of 3911 patients given intravenous dipyridamole as an adjunct to thallium myocardial perfusion imaging, two types of serious adverse events were reported:

1. four cases of myocardial infarction (0.1%), two fatal (0.05%) and two non-fatal (0.05%) and

2. six cases of severe bronchospasm (0.2%).

Although the incidence of these serious adverse events was small (0.3%, 10 of 3911), the potential clinical information to be gained through use of intravenous dipyridamole thallium imaging (see INDICATIONS AND USAGE noting the rate of false positive and false negative results) must be weighed against the risk to the patient. Patients with a history of unstable angina may be at a greater risk for severe myocardial ischemia. Patients with a history of asthma may be at a greater risk for bronchospasm during Dipyridamole Injection use. When thallium myocardial perfusion imaging is performed with intravenous dipyridamole, parenteral aminophylline should be readily available for relieving adverse events such as bronchospasm or chest pain. Vital signs should be monitored during, and for 10-15 minutes following, the intravenous infusion of dipyridamole and an electrocardiographic tracing should be obtained using at least one chest lead. Should severe chest pain or bronchospasm occur, parenteral aminophylline may be administered by slow intravenous injection (50-100 mg over 30-60 seconds) in doses ranging from 50 to 250 mg. In the case of severe hypotension, the patient should be placed in a supine position with the head tilted down if necessary, before administration of parenteral aminophylline. If 250 mg of aminophylline does not relieve chest pain symptoms within a few minutes, sublingual nitroglycerin may be administered. If chest pain continues despite use of aminophylline and nitroglycerin, the possibility of myocardial infarction should be considered. If the clinical condition of a patient with an adverse event permits a one-minute delay in the administration of parenteral aminophylline, thallium-201 may be injected and allowed to circulate for one minute before the injection of aminophylline. This will allow initial thallium perfusion imaging to be performed before reversal of the pharmacologic effects of dipyridamole on the coronary circulation.

Precautions

See WARNINGS.

Drug Interactions

Oral maintenance theophylline and other xanthine derivatives such as caffeine may abolish the coronary vasodilatation induced by intravenous Dipyridamole Injection administration. This could lead to a false negative thallium imaging result (see CLINICAL PHARMACOLOGY – Mechanism of Action). Myasthenia gravis patients receiving therapy with cholinesterase inhibitors may experience worsening of their disease in the presence of dipyridamole.

Carcinogenesis, Mutagenesis, Impairment of Fertility

In studies in which dipyridamole was administered in the feed at doses of up to 75 mg/kg/day (9.4 times1 the maximum recommended daily human oral dose) in mice (up to 128 weeks in males and up to 142 weeks in females) and rats (up to 111 weeks in males and females), there was no evidence of drug-related carcinogenesis. Mutagenicity tests of dipyridamole with bacterial and mammalian cell systems were negative. There was no evidence of impaired fertility when dipyridamole was administered to male and female rats at oral doses up to 500 mg/kg/day (63 times 1. the maximum recommended daily human oral dose). A significant reduction in number of corpora lutea with consequent reduction in implantations and live fetuses was, however, observed at 1250 mg/kg/day.

1Calculation based on assumed body weight of 50kg

Pregnancy

Teratogenic Effects – Pregnancy Category B

Reproduction studies performed in mice and rats at daily oral doses of up to 125 mg/kg (15.6 times1 the maximum recommended daily human oral dose) and in rabbits at daily oral doses of up to 20 mg/kg (2.5 times1 the maximum recommended daily human oral dose) have revealed no evidence of impaired embryonic development due to dipyridamole. There are, however, no adequate and wellcontrolled studies in pregnant women. Because animal reproduction studies are not always predictive of human responses, this drug should be used during pregnancy only if clearly needed.

1Calculation based on assumed body weight of 50kg

Nursing MothersDipyridamole is excreted in human milk.

Pediatric Use

Safety and effectiveness in pediatric patients have not been established.

Adverse Reactions

Adverse reaction information concerning intravenous Dipyridamole Injection is derived from a study of 3911 patients in which intravenous dipyridamole was used as an adjunct to thallium myocardial perfusion imaging and from spontaneous reports of adverse reactions and the published literature.
Serious adverse events (cardiac death, fatal and non-fatal myocardial infarction, ventricular fibrillation, asystole, sinus node arrest, symptomatic ventricular tachycardia, stroke, transient cerebral ischemia, seizures, anaphylactoid reaction and bronchospasm) are described above (seeWARNINGS).
In a study of 3911 patients, the most frequent adverse reactions were: chest pain/angina pectoris (19.7%), electrocardiographic changes (most commonly ST-T changes) (15.9%), headache (12.2%) and dizziness (11.8%). Adverse reactions occurring in greater than 1% of the patients in the study are shown in the following table:

Less common adverse reactions occurring in 1% or less of the patients within the study included:

Cardiovascular System
Electrocardiographic abnormalities unspecified (0.8%), arrhythmia unspecified (0.6%), palpitation (0.3%), ventricular tachycardia (0.2%-see WARNINGS), bradycardia (0.2%), myocardial infarction (0.1%–see WARNINGS), AV block (0.1%), syncope (0.1%), orthostatic hypotension (0.1%), atrial fibrillation (0.1%), supraventricular tachycardia (0.1%), ventricular arrhythmia unspecified (0.03%–see WARNINGS), heart block unspecified (0.03%), cardiomyopathy (0.03%), edema (0.03%).
Central and Peripheral Nervous System
Hypothesia (0.5%), hypertonia (0.3%), nervousness/anxiety (0.2%), tremor (0.1%), abnormal coordination (0.03%), somnolence (0.03%), dysphonia (0.03%), migraine (0.03%), vertigo (0.03%).
Gastrointestinal System
Dyspepsia (1%), dry mouth (0.8%), abdominal pain (0.7%), flatulence (0.6%), vomiting (0.4%), eructation (0.1%), dysphagia (0.03%), tenesmus (0.03%), appetite increase (0.03%).
Respiratory System
Pharyngitis (0.3%), bronchospasm (0.2%–see WARNINGS), hyperventilation (0.1%), rhinitis (0.1%), coughing (0.03%), pleural pain (0.03%).
Other
Myalgia (0.9%), back pain (0.6%), injection site reaction unspecified (0.4%), diaphoresis (0.4%), asthenia (0.3%), malaise (0.3%), arthralgia (0.3%), injection site pain (0.1%), rigor (0.1%), earache (0.1%), tinnitus (0.1%), vision abnormalities unspecified (0.1%), dysgeusia (0.1%), thirst (0.03%), depersonalization (0.03%), eye pain (0.03%), renal pain (0.03%), perineal pain (0.03%), breast pain (0.03%), intermittent claudication (0.03%), leg cramping (0.03%). In additional postmarketing experience, there have been rare reports of allergic reaction including urticaria, pruritus, dermatitis and rash.

Overdosage

No cases of overdosage in humans have been reported. It is unlikely that overdosage will occur because of the nature of use (i.e., single intravenous administration in controlled settings). See WARNINGS.

Dosage and Administration

The dose of intravenous Dipyridamole Injection as an adjunct to thallium myocardial perfusion imaging should be adjusted according to the weight of the patient. The recommended dose is 0.142 mg/kg/min (0.57 mg/kg total) infused over 4 minutes. Although the maximum tolerated dose has not been determined, clinical experience suggests that a total dose beyond 60 mg is not needed for any patient.
Prior to intravenous administration, Dipyridamole Injection should be diluted in at least a 1:2 ratio with sodium chloride injection 0.45%, sodium chloride injection 0.9% or dextrose injection 5% for a total volume of approximately 20 to 50 mL. Infusion of undiluted dipyridamole may cause local irritation. Thallium-201 should be injected within 5 minutes following the 4-minute infusion of dipyridamole. Do not mix Dipyridamole Injection with other drugs in the same syringe or infusion container.
Parenteral drug products should be inspected visually for particulate matter and discoloration prior to administration, whenever solution and container permit.

How Supplied

Dipyridamole Injection, USP is available in:
10 mL (50 mg/10 mL) SINGLE DOSE vial packaged in 5s (NDC 0641-2569-44)

Storage
PROTECT FROM LIGHT: Keep covered in carton until time of use. Store between 15° to 25°C (59° to 77°F). Avoid freezing.

To report SUSPECTED ADVERSE REACTIONS, contact Hikma Pharmaceuticals USA Inc. at 1-877-845-0689, or the FDA at 1-800-FDA-1088 or www.fda.gov/medwatch.

For Product Inquiry call 1-877-845-0689.

Manufactured by:
Hikma Pharmaceuticals USA Inc.
Berkeley Heights, NJ 07922

Revised December 2019

462-341-03

Product repackaged by: Henry Schein, Inc., Bastian, VA 24314
From Original Manufacturer/Distributor's NDC and Unit of Sale | To Henry Schein Repackaged Product NDC and Unit of Sale | Total Strength/Total Volume (Concentration) per unit
NDC 0641-2569-44 10 mL SINGLE DOSE vials packaged in 5s | NDC 0404-9852-10 1 10 mL SINGLE DOSE vial in a bag (Vial bears NDC 0641-2569-41) | 50 mg/10 mL